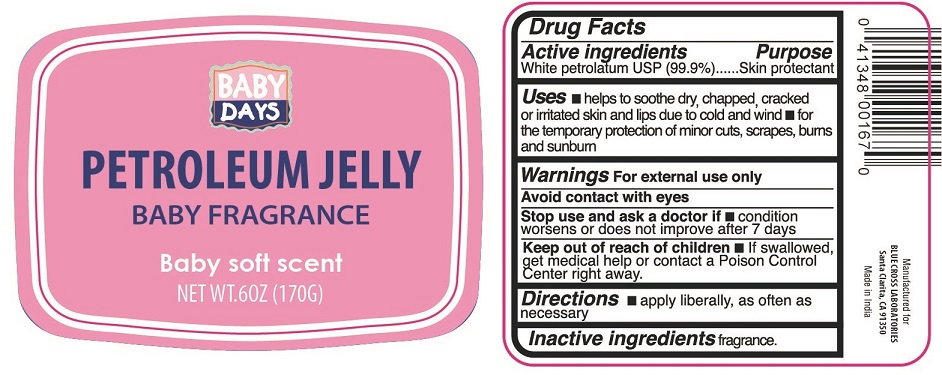 DRUG LABEL: BABY SOFT SCENT PETROLEUM
NDC: 22431-706 | Form: JELLY
Manufacturer: Blue Cross Laboratories, Inc.
Category: otc | Type: HUMAN OTC DRUG LABEL
Date: 20190307

ACTIVE INGREDIENTS: PETROLATUM 0.99 g/1 g

Active ingredient

White petrolatum USP (99.9 %)

Purpose

Skin protectant

Uses

- helps to soothe dry, chapped, cracked or irritated skin and lip due to cold and wind
- for the temporary protection of minor cuts, scrapes, burns and sunburn

Warnings

For external use only

Avoid contact with eyes

Stop use and ask a doctor if condition worsens or does not improve after 7 days.

Keep out of reach of children if swallowed, get medical help or contact a Poison Control Center right away.

Directions

- apply liberally, as often as necessary

Inactive ingredients

Fragrance

PRINCIPAL DISPLAY PANEL

BABY SOFT SCENT PETROLEUM JELLY
Skin Protectant
NET WT. 6 OZ (170 g)